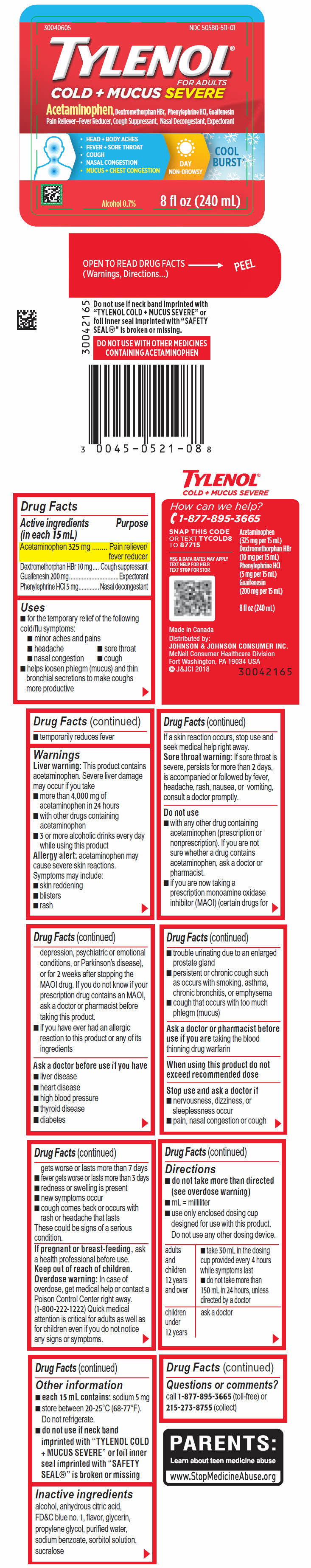 DRUG LABEL: TYLENOL Cold Plus Mucus Severe
NDC: 50580-511 | Form: SOLUTION
Manufacturer: Kenvue Brands LLC
Category: otc | Type: HUMAN OTC DRUG LABEL
Date: 20241107

ACTIVE INGREDIENTS: ACETAMINOPHEN 325 mg/15 mL; DEXTROMETHORPHAN HYDROBROMIDE 10 mg/15 mL; GUAIFENESIN 200 mg/15 mL; PHENYLEPHRINE HYDROCHLORIDE 5 mg/15 mL
INACTIVE INGREDIENTS: ALCOHOL; ANHYDROUS CITRIC ACID; FD&C BLUE NO. 1; GLYCERIN; PROPYLENE GLYCOL; WATER; SODIUM BENZOATE; SORBITOL SOLUTION; SUCRALOSE

TYLENOL Cold + Mucus Severe

Drug Facts

ACTIVE INGREDIENT

Active ingredients (in each 15 mL) | Purpose
Acetaminophen 325 mg | Pain reliever/fever reducer
Dextromethorphan HBr 10 mg | Cough suppressant
Guaifenesin 200 mg | Expectorant
Phenylephrine HCl 5 mg | Nasal decongestant

Uses

- for the temporary relief of the following cold/flu symptoms:
  - minor aches and pains
  - headache
  - sore throat
  - nasal congestion
  - cough
- helps loosen phlegm (mucus) and thin bronchial secretions to make coughs more productive
- temporarily reduces fever

Warnings

Liver warning

This product contains acetaminophen. Severe liver damage may occur if you take

- more than 4,000 mg of acetaminophen in 24 hours
- with other drugs containing acetaminophen
- 3 or more alcoholic drinks every day while using this product

Allergy alert: acetaminophen may cause severe skin reactions.

Symptoms may include:

- skin reddening
- blisters
- rash

If a skin reaction occurs, stop use and seek medical help right away.

Sore throat warning

If sore throat is severe, persists for more than 2 days, is accompanied or followed by fever, headache, rash, nausea, or vomiting, consult a doctor promptly.

Do not use

- with any other drug containing acetaminophen (prescription or nonprescription). If you are not sure whether a drug contains acetaminophen, ask a doctor or pharmacist.
- if you are now taking a prescription monoamine oxidase inhibitor (MAOI) (certain drugs for depression, psychiatric or emotional conditions, or Parkinson's disease), or for 2 weeks after stopping the MAOI drug. If you do not know if your prescription drug contains an MAOI, ask a doctor or pharmacist before taking this product.
- if you have ever had an allergic reaction to this product or any of its ingredients

Ask a doctor before use if you have

- liver disease
- heart disease
- high blood pressure
- thyroid disease
- diabetes
- trouble urinating due to an enlarged prostate gland
- persistent or chronic cough such as occurs with smoking, asthma, chronic bronchitis, or emphysema
- cough that occurs with too much phlegm (mucus)

Ask a doctor or pharmacist before use if you are taking the blood thinning drug warfarin

When using this product do not exceed recommended dose

Stop use and ask a doctor if

- nervousness, dizziness, or sleeplessness occur
- pain, nasal congestion or cough gets worse or lasts more than 7 days
- fever gets worse or lasts more than 3 days
- redness or swelling is present
- new symptoms occur
- cough comes back or occurs with rash or headache that lasts

These could be signs of a serious condition.

PREGNANCY OR BREAST FEEDING

If pregnant or breast-feeding, ask a health professional before use.

Keep out of reach of children.

Overdose warning

In case of overdose, get medical help or contact a Poison Control Center right away. (1-800-222-1222) Quick medical attention is critical for adults as well as for children even if you do not notice any signs or symptoms.

Directions

- do not take more than directed (see overdose warning)
- mL = milliliter
- use only enclosed dosing cup designed for use with this product. Do not use any other dosing device.

adults and children 12 years and over | - take 30 mL in the dosing cup provided every 4 hours while symptoms last - do not take more than 150 mL in 24 hours, unless directed by a doctor
children under 12 years | ask a doctor

Other information

- each 15 mL contains: sodium 5 mg
- store between 20-25°C (68-77°F). Do not refrigerate.
- do not use if neck band imprinted with "TYLENOL COLD + MUCUS SEVERE" or foil inner seal imprinted with "SAFETY SEAL®" is broken or missing

Inactive ingredients

alcohol, anhydrous citric acid, FD&C blue no. 1, flavor, glycerin, propylene glycol, purified water, sodium benzoate, sorbitol solution, sucralose

Questions or comments?

call 1-877-895-3665 (toll-free) or 215-273-8755 (collect)

PRINCIPAL DISPLAY PANEL

NDC 50580-511-01

TYLENOL®
FOR ADULTS

COLD + MUCUS SEVERE

Acetaminophen, Dextromethorphan HBr, Phenylephrine HCl, Guaifenesin
Pain Reliever–Fever Reducer, Cough Suppressant, Nasal Decongestant, Expectorant

- HEAD + BODY ACHES
- FEVER + SORE THROAT
- COUGH
- NASAL CONGESTION
- MUCUS + CHEST CONGESTION

DAY
NON-DROWSY

COOL
BURST ®

Alcohol 0.7%

8 fl oz (240 mL)